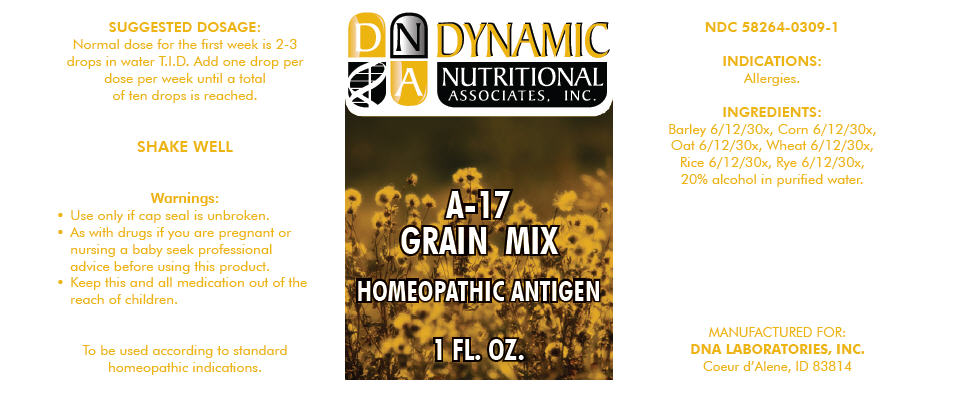 DRUG LABEL: A-17
NDC: 58264-0309 | Form: SOLUTION
Manufacturer: DNA Labs, Inc.
Category: homeopathic | Type: HUMAN OTC DRUG LABEL
Date: 20250109

ACTIVE INGREDIENTS: BARLEY 30 [hp_X]/1 mL; CORN 30 [hp_X]/1 mL; OAT 30 [hp_X]/1 mL; WHITE RICE 30 [hp_X]/1 mL; RYE 30 [hp_X]/1 mL; WHEAT 30 [hp_X]/1 mL
INACTIVE INGREDIENTS: ALCOHOL; WATER

A-17

NDC 58264-0309-1

INDICATIONS

PURPOSE

Allergies.

INGREDIENTS

INACTIVE INGREDIENT

Barley 6/12/30x, Corn 6/12/30x, Oat 6/12/30x, Wheat 6/12/30x, Rice 6/12/30x, Rye 6/12/30x, 20% alcohol in purified water.

SUGGESTED DOSAGE

Normal dose for the first week is 2-3 drops in water T.I.D. Add one drop per dose per week until a total of ten drops is reached.

STORAGE AND HANDLING

SHAKE WELL

Warnings

- Use only if cap seal is unbroken.

PREGNANCY OR BREAST FEEDING

- As with drugs if you are pregnant or nursing a baby seek professional advice before using this product.

KEEP OUT OF REACH OF CHILDREN

- Keep this and all medication out of the reach of children.

To be used according to standard homeopathic indications.

PRINCIPAL DISPLAY PANEL - 1 FL. OZ. Bottle Label

DYNAMIC
NUTRITIONAL
ASSOCIATES, INC.

A-17
GRAIN MIX

HOMEOPATHIC ANTIGEN

1 FL. OZ.